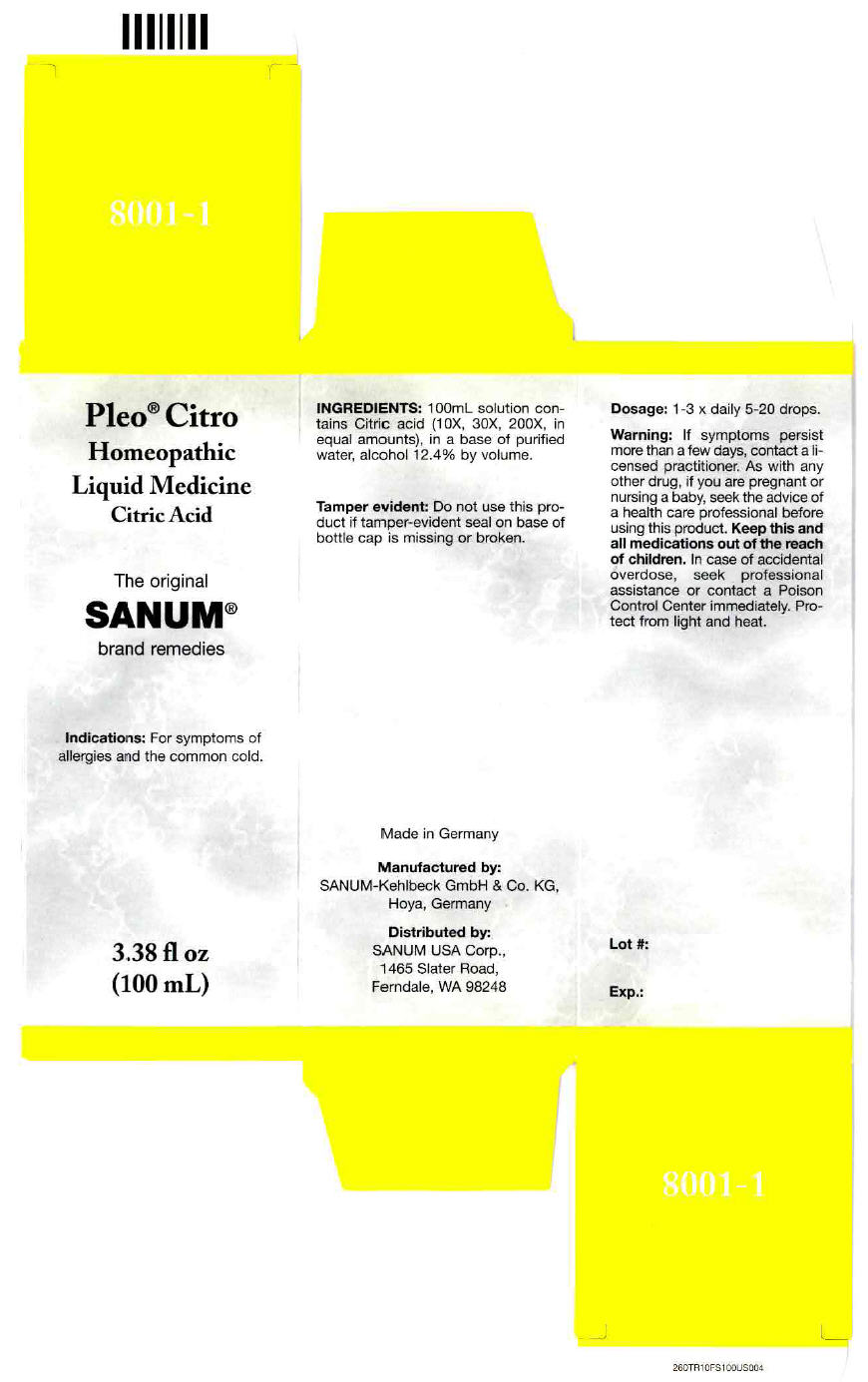 DRUG LABEL: Pleo Citro
NDC: 60681-8001 | Form: LIQUID
Manufacturer: Sanum Kehlbeck GmbH & Co. KG
Category: homeopathic | Type: HUMAN OTC DRUG LABEL
Date: 20111107

ACTIVE INGREDIENTS: citric acid monohydrate 200 [hp_X]/100 mL
INACTIVE INGREDIENTS: water; alcohol

Pleo® Citro

PURPOSE

Homeopathic
Liquid Medicine
Citric Acid

3.38 fl oz
(100 mL)

Indications

For symptoms of allergies and the common cold.

INGREDIENTS

INACTIVE INGREDIENT

100mL solution contains Citric acid (10X, 30X, 200X, in equal amounts), in a base of purified water, alcohol 12.4% by volume.

Tamper evident

Do not use this product if tamper-evident seal on base of bottle cap is missing or broken.

Dosage

1-3 × daily 5-20 drops.

Warning

If symptoms persist more than a few days, contact a licensed practitioner. As with any other drug, if you are pregnant or nursing a baby, seek the advice of a health care professional before using this product.

KEEP OUT OF REACH OF CHILDREN

Keep this and all medications out of the reach of children. In case of accidental overdose, seek professional assistance or contact a Poison Control Center immediately.

STORAGE AND HANDLING

Protect from light and heat.

Made in Germany

Manufactured by:
SANUM-Kehlbeck GmbH & Co. KG,
Hoya, Germany

Distributed by:
SANUM USA Corp.,
1465 Slater Road,
Ferndale, WA 98248

PRINCIPAL DISPLAY PANEL - 100 mL Carton

Pleo® Citro
Homeopathic
Liquid Medicine
Citric Acid

The original
SANUM®
brand remedies

Indications: For symptoms of
allergies and the common cold.

3.38 fl oz
(100 mL)